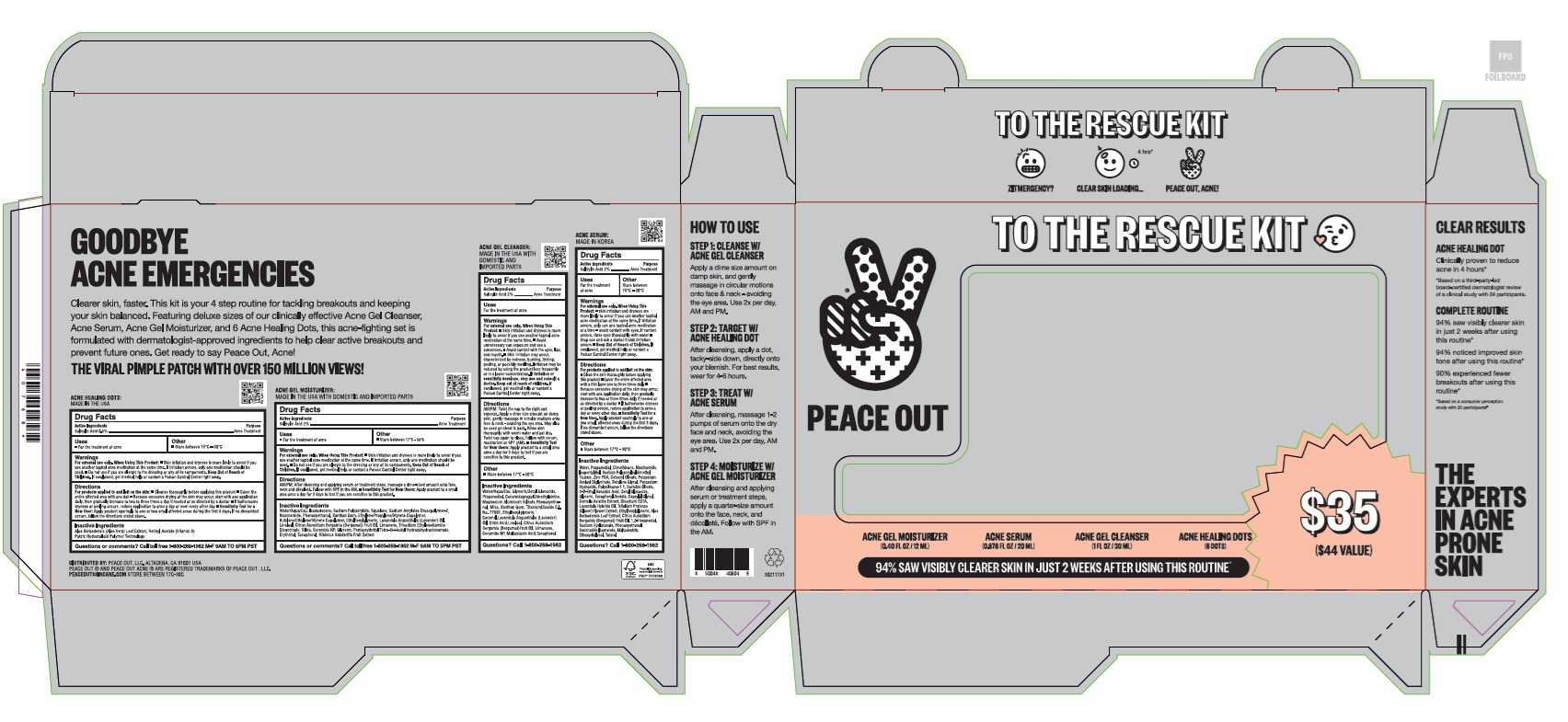 DRUG LABEL: Peace Out To The Rescue Kit
NDC: 71494-104 | Form: KIT | Route: TOPICAL
Manufacturer: Peace Out Inc.
Category: otc | Type: HUMAN OTC DRUG LABEL
Date: 20250508

ACTIVE INGREDIENTS: SALICYLIC ACID 20 mg/1 mL; SALICYLIC ACID 20 mg/1 mL; SALICYLIC ACID 0.359 mg/1 1; SALICYLIC ACID 20 mg/1 mL
INACTIVE INGREDIENTS: CITRIC ACID MONOHYDRATE; MALTOBIONIC ACID; BERGAMOT OIL; TOCOPHEROL; LIMONENE, (+)-; DECYL GLUCOSIDE; PROPANEDIOL; CI 77891; ETHYLHEXYLGLYCERIN; LINALOOL, (+)-; LAVENDER OIL; COCAMIDOPROPYL DIMETHYLAMINE; MAGNESIUM ALUMINUM SILICATE; XANTHAN GUM; CERAMIDE NP; CARAMEL; WATER; PHENOXYETHANOL; MICA; GLYCERIN; ISODODECANE; WATER; SODIUM ACRYLATES CROSSPOLYMER-2; SILICON DIOXIDE; PENTAERYTHRITYL TETRA-DI-T-BUTYL HYDROXYHYDROCINNAMATE; TOCOPHEROL; SODIUM POLYACRYLATE (2500000 MW); SQUALANE; LAVENDER OIL; XANTHAN GUM; CERAMIDE NP; NIACINAMIDE; GLYCERIN; ERYTHRITOL; PHENOXYETHANOL; LINALOOL, (+)-; BERGAMOT OIL; ETHYLHEXYLGLYCERIN; LIMONENE, (+)-; TRISODIUM ETHYLENEDIAMINE DISUCCINATE; VITAMIN A ACETATE; ALOE VERA LEAF; BUTYLENE GLYCOL; ZINC PCA; CETEARYL OLIVATE; ETHYLHEXYLGLYCERIN; TRIFOLIUM PRATENSE FLOWER; .ALPHA.-TOCOPHEROL ACETATE; GLYCERIN; EDETATE DISODIUM; PHENOXYETHANOL; DECYL GLUCOSIDE; 3-O-ETHYL ASCORBIC ACID; POTASSIUM AZELOYL DIGLYCINATE; SORBITAN OLIVATE; CAPRYLYL GLYCOL; SODIUM POLYACRYLOYLDIMETHYL TAURATE; DIMETHICONE; NIACINAMIDE; HYALURONATE SODIUM; CENTELLA ASIATICA; SACCHARIDE ISOMERATE; WATER; ALOE VERA LEAF; POTASSIUM HYDROXIDE; PROPANEDIOL; ISOPENTYLDIOL; DIMETHICONE/VINYL DIMETHICONE CROSSPOLYMER (SOFT PARTICLE); MALTODEXTRIN; 1,2-HEXANEDIOL; LAVANDIN OIL; TOTAROL; BERGAMOT OIL; ETHOXYDIGLYCOL

Peace Out To The Rescue Kit

Active Ingredients

Dots: Salicylic Acid 0.5%

Serum/Cleanser/Moisturizer: Salicylic Acid 2%

Purpose

Acne Treatment

Uses

- For the treatment of acne

Other

Dots:

- Store between 15C - 30C

Serum/Cleanser/Moisturizer:

- Store between 17C - 30C

Warnings

For external use only

When Using This Product

Dots/Moisturizer

- Skin irritation and dryness is more likely to occur if you use another topical acne medication at the same time. If irritation occurs, only one medication should be used.
- Do not use if you are allergic to the dressing or any of its components.

Cleaner

- Skin irritation and dryness is more likely to occur if you use another topical acne medication at the same time.
- Avoid unnecessary sun exposure and use a sunscreen.
- Avoid contact with the eyes, lips, and mouth.
- Skin irritation may occur, characterized by redness, burning, itching, peeling, or possibly swelling. Irritation may be reduced by using the product less frequently or in a lower concentration . If irritation or sensitivity develops, stop use and consult a doctor.

Serum

- skin irritation and dryness are more likely to occur if you use another topical acne medication at the same time. If irritation occurs, only use one topical acne medication at a time.
- avoid contact with eyes. If contact occurs, rinse eyes thoroughly with water
- Stop use and ask a doctor if skin irritation occurs

Keep Out of Reach of Children.

If swallowed, get medical help or contact a Poison Control Center right away.

Directions

Dots:

For products applied to and left on the skin:

- Cleanse thoroughly before applying this product
- Cover the entire affected area with one dot
- Because excessive drying of the skin may occur, start with one application daily, then gradually increase to two or three times a daily if needed or as directed by a doctor
- If bothersome dryness or peeling occurs, reduce application to once a day or even every other day
- Sensitivity Test for a New User: Apply product sparingly to one or two small affected areas during the first 3 days. If no discomfort occurs, follow the directions stated above.

Serum:

For products applied to and left on the skin:

- Clean the skin thoroughly before applying this product
- Cover the entire affected area with a thin layer one to three times daily
- Because excessive drying of the skin may occur, start with one application daily, then gradually increase to two or three times daily if needed or as directed by a doctor
- If bothersome dryness or peeling occurs, reduce application to once a day or every other day
- Sensitivity Test for a New User: Apply product sparingly to one or two small affected areas during the first 3 days. If no discomfort occurs, follow the directions stated above.

Moisturizer:

- AM/PM: After cleansing and applying serum or treatment steps, massage a dime-sized amount onto face, neck and decollete. Follw with SPF in the AM.
- Sensitivity Test for New Users: Apply product to a small area once a day for 3 days to test if you are sensitive to this product.

Cleanser:

- AM/PM: Twist the cap to the right and squeeze. Apply a dime size amount on damp skin, gently massage in circular motions onto face and neck avoiding the eye area. May also be used on chest and back. Rinse skin thoroughly with warm water and pat dry. Twist cap again to close. Follow with serum, moisturizer or SPF (AM).
- Sensitivity Test for New Users: Apply product to a small area once a day for 3 days to test if you are sensitive to this product.

Inactive Ingredients

Dots:

Aloe Barbadensis (Aloe Vera) Leaf Extract, Retinyl Acetate (Vitamin A)
Patch: Hydrocolloid Polymer Technology

Serum:

Water, Propanediol, Dimethicone, Niacinamide, Isopentyldiol, Sodium Polyacryloyldimethyl Taurate, Zinc PCA, Cetearyl Olivate, Potassium Azeloyl Diglycinate, Butylene Glycol, Potassium Hydroxide, Polysilicone-11, Sorbitan Olivate, 3-O-Ethyl Ascorbic Acid, Decyl Glucoside, Glycerin, Tocopheryl Acetate, Caprylyl Glycol, Centella Asiatica Extract, Disodium EDTA, Lavandula Hybrida Oil, Trifolium Pratense (Clover) Flower Extract, Ethylhexylglycerin, Aloe Barbadensis Leaf Extract, Citrus Aurantium Bergamia (Bergamot) Fruit Oil, 1,2-Hexanediol, Sodium Hyaluronate, Phenoxyethanol, Saccharide Isomerate, Maltodextrin, Ethoxydiglycol, Totarol

Moisturizer:

Water/Aqua/Eau, Isododecane, Sodium Polyacrylate, Squalane, Sodium Acrylates Crosspolymer-2, Niacinamide, Phenoxyethanol, Xanthan Gum, Ethylene/Propylene/Styrene Copolymer, Butylene/Ethylene/Styrene Copolymer, Ethylhexylglycerin, Lavandula Angustifolia (Lavender) Oil, Linalool, Citrus Aurantium Bergamia (Bergamot) Fruit Oil, Limonene, Trisodium Ethylenediamine Disuccinate, Silica, Ceramide NP, Glycerin, Pentaerythrityl Tetra-di-t-butyl Hydroxyhydrocinnamate, Erythritol, Tocopherol, Hibiscus Sabdariffa Fruit Extract

Cleanser:

Water/Aqua/Eau, Glycerin, Decyl Glucoside, Propanediol, Cocamidopropyl Dimethylamine, Magnesium Aluminum Silicate, Phenoxyethano, Mica, Xanthan Gum, Titanium Dioxide CI 77891, Ethylhexylglycerin, Caramel, Lavandula Angustifolia (Lavender) Oil, Citric Acid, Linalool, Citrus Aurantium Bergamia (Bergamot) Fruit Oil, Limonene, Ceramide NP, Maltobionic Acid, Tocopherol

Questions?

Call 1-800-268-1962

Company Information

Distributed by: Peace Out, LLC. Altadena, CA 91001 USA